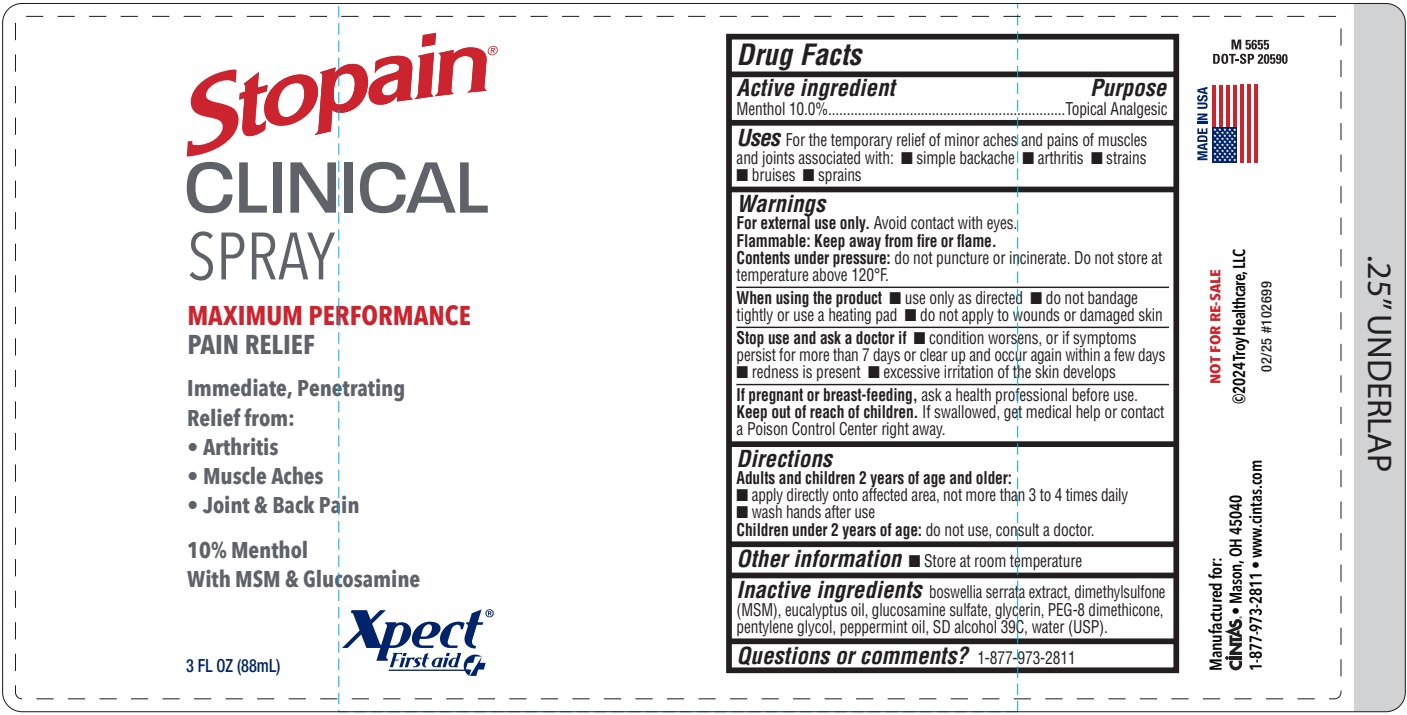 DRUG LABEL: Xpect Stopain Clinical
NDC: 42961-257 | Form: SPRAY
Manufacturer: Cintas Corporation
Category: otc | Type: HUMAN OTC DRUG LABEL
Date: 20250521

ACTIVE INGREDIENTS: MENTHOL 100 mg/1 mL
INACTIVE INGREDIENTS: BOSWELLIA SERRATA OIL; DIMETHYL SULFONE; EUCALYPTUS OIL; GLUCOSAMINE SULFATE; GLYCERIN 1,2-DIMETHYL ETHER; PEG-8 DIMETHICONE; PENTYLENE GLYCOL; PEPPERMINT OIL; ALCOHOL; WATER

Xpect Stopain Clinical Maximum Performance Pain Relief

Active ingredient

Menthol 10.0%

Purpose

Topical Analgesic

Uses

For the temporary relief of minor aches and pains of muscles and joints associated with:

- simple backache
- arthritis
- strains
- bruises
- sprains

Warnings

For external use only. Avoid contact with eyes.

Flammable: Keep away from fire or flame.

Contents under pressure: do not puncture or incinerate. Do not store at temperature above 120°F.

When using the product

- use only as directed
- do not bandage tightly or use a heating pad
- do not apply to wounds or damaged skin

Stop use and ask a doctor if

- condition worsens, or if symptoms persist for more than 7 days or clear up and occur again within a few days
- redness is present
- excessive irritation of the skin develops

PREGNANCY OR BREAST FEEDING

If pregnant or breast-feeding, ask a health professional before use.

Keep out of reach of children. If swallowed, get medical help or contact a Poison Control Center right away.

Directions

Adults and children 2 years of age and older:

- apply directly onto affected area, not more than 3 to 4 times daily
- wash hands after use

Children under 2 years of age: do not use, consult a doctor

Other information

- Store at room temperature

Inactive ingredients

boswellia serrata extract, dimethylsulfone (MSM), eucalyptus oil, glucosamine sulfate, glycerin, PEG-8 dimethicone, pentylene glycol, peppermint oil, SD alcohol 39C, water (USP).

Questions or comments?

1-877-973-2811

Principal Dispay 42961-257-01

Xpect Stopain Clinical Spray Label